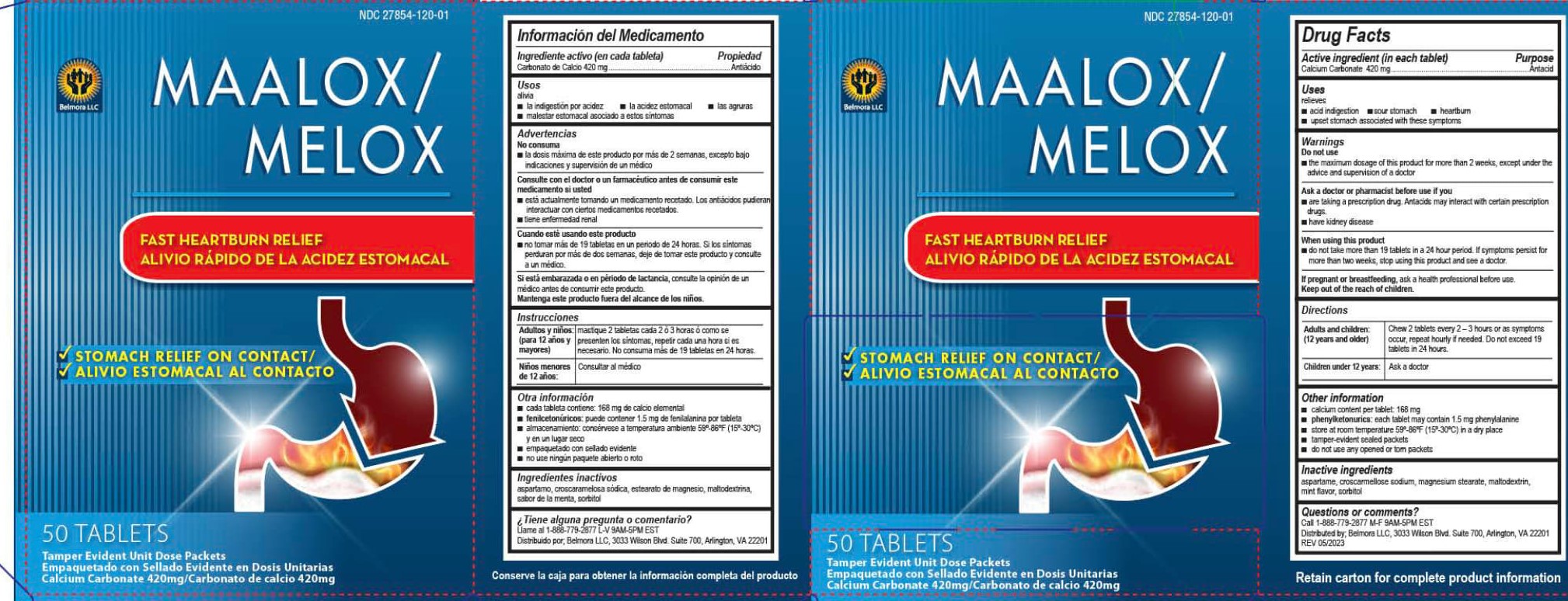 DRUG LABEL: Belmora MELOX AGRURA
NDC: 27854-120 | Form: TABLET, CHEWABLE
Manufacturer: Belmora, LLC
Category: otc | Type: HUMAN OTC DRUG LABEL
Date: 20250908

ACTIVE INGREDIENTS: CALCIUM CARBONATE 420 mg/1 1
INACTIVE INGREDIENTS: CROSCARMELLOSE SODIUM; SORBITOL; MAGNESIUM STEARATE; ASPARTAME; MALTODEXTRIN

Belmora Maalox / Melox

Drug Facts

Active ingredient (in each tablet)

Calcium Carbonate 420 mg

Purpose

Antacid

Uses

relieves

■ acid indigestion

■ sour stomach

■ heartburn

■ upset stomach associated with these symptoms

Warnings

Do not use

■ the maximum dosage of this product for more than 2 weeks, except under the advice and supervision of a doctor

Ask a doctor or pharmacist before use if you

■ are taking a prescription drug. Antacids may interact with certain prescription drugs.

■ have kidney disease

When using this product

■ do not take more than 19 tablets in a 24 hour period. If symptoms persist for more than two weeks, stop using this product and see a doctor.

PREGNANCY OR BREAST FEEDING

If pregnant or breast feeding, ask a health professional before use.

Keep out of the reach of children.

Directions

Adults and children: (12 years and older) Chew 2 tablets every 2-3 hours or as symptoms occur, repeat hourly if needed.

Do not exceed 19 tablets in 24 hours.

Children under 12 years: ask a doctor

Other information

■ calcium content per tablet: 168 mg

■ phenylketonurics: each tablet may contain1.5 mg phenylalanine

■ store at room temperature 59-86ºF (15-30ºC) in a dry place

■ tamper-evident sealed packets

■ do not use any opened or torn packets

Inactive ingredients

aspartame, croscarmellose sodium, magnesium stearate, maltodextrin, mint flavor, sorbitol

Questions or comments?

Call 1-800-779-2877 M-F 9AM-5PM EST

Distributed by: Belmora LLC, 3033 Wilson Blvd. Suite 700, Arlington, VA 22201

REV 02/2022

Belmora Maalox / Melox

NDC 27854-120-01

Belmora LLC

Maalox /

Melox

FAST HEARTBURN RELIEF

ALIVIO RÁPIDO DE LA ACIDEX ESTOMACAL

√ STOMACH RELIEF ON CONTACT /

√ ALIVO ESTOMACAL AL CONTACTO

100 Tablets/50-Dual Packets/1 Tablets per Packet

Tamper Evident Unit Dose Packets/Empacquetado con Sellado Evidente en Dosis Unitarias

Calcium Carbonate 420mg/Carbonato de calcio 420mg